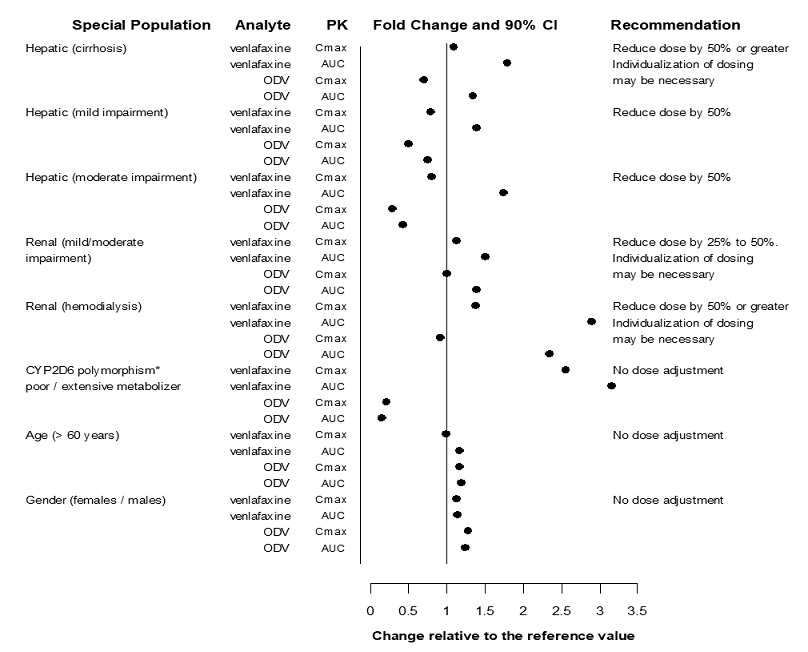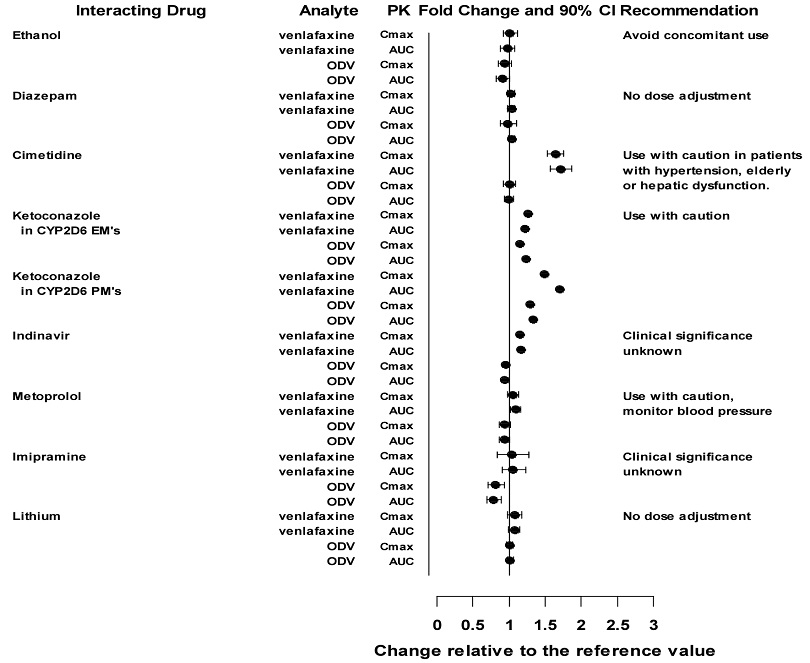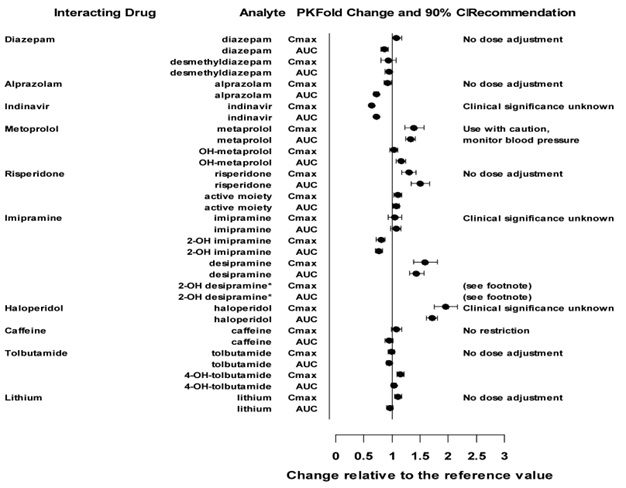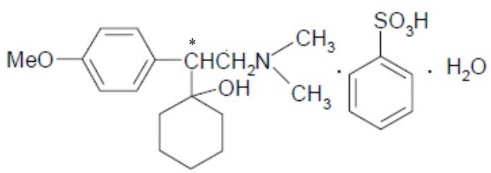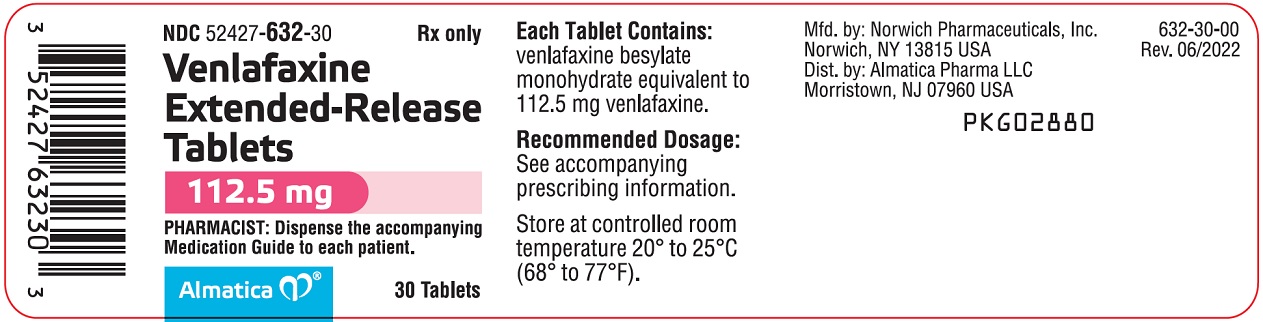 DRUG LABEL: venlafaxine
NDC: 52427-632 | Form: TABLET, EXTENDED RELEASE
Manufacturer: Almatica Pharma LLC
Category: prescription | Type: HUMAN PRESCRIPTION DRUG LABEL
Date: 20251009

ACTIVE INGREDIENTS: VENLAFAXINE BESYLATE MONOHYDRATE 112.5 mg/1 1
INACTIVE INGREDIENTS: AMMONIO METHACRYLATE COPOLYMER TYPE A; HYPROMELLOSE, UNSPECIFIED; LACTOSE MONOHYDRATE; MAGNESIUM STEARATE; MICROCRYSTALLINE CELLULOSE; POLYETHYLENE GLYCOL, UNSPECIFIED; POVIDONE K30; SILICON DIOXIDE; DIMETHICONE; TALC; TITANIUM DIOXIDE; TRIACETIN; AMMONIA; FERROSOFERRIC OXIDE; BUTYL ALCOHOL; ISOPROPYL ALCOHOL; PROPYLENE GLYCOL; SHELLAC

HIGHLIGHTS OF PRESCRIBING INFORMATION

These highlights do not include all the information needed to use VENLAFAXINE EXTENDED-RELEASE TABLETS safely and effectively. See full prescribing information for VENLAFAXINE EXTENDED-RELEASE TABLETS.
VENLAFAXINE extended-release tablets, for oral use
Initial U.S. Approval: 1993

RECENT MAJOR CHANGES

Warnings and Precautions (5.2, 5.4) | 8/2023

WARNING: SUICIDAL THOUGHTS AND BEHAVIORS

See full prescribing information for complete boxed warning.

- Increased risk of suicidal thinking and behavior in pediatric and young adult patients taking antidepressants. Closely monitor all antidepressant-treated patients for clinical worsening and emergence of suicidal thoughts and behaviors (5.1).
- Venlafaxine Extended-Release Tablets are not approved for use in pediatric patients (8.4)

1 INDICATIONS AND USAGE

Venlafaxine Extended-Release Tablets are a serotonin and norepinephrine reuptake inhibitor (SNRI) indicated in adults for the treatment of:

- Major Depressive Disorder (MDD) (1)
- Generalized Anxiety Disorder (GAD) (1)

2 DOSAGE AND ADMINISTRATION

- Do not initiate treatment with Venlafaxine Extended-Release Tablets. Use another venlafaxine extended-release product for initial dosage, titration, and dosages below 112.5 mg once daily (2.1).
- Take once daily with food. Swallow tablets whole with fluid. Do not divide, crush, chew, or place in water (2.1).
- Venlafaxine Extended-Release Tablets can be initiated at 112.5 mg once daily in patients who have received at least 75 mg of another venlafaxine extended-release product for at least 4 days (2.2, 2.3).
- Maximum recommended dosage is 225 mg once daily (2.2, 2.3).
- When discontinuing treatment, reduce the dose gradually. Gradual dosage reduction will require the use of another venlafaxine extended-release product (2.8, 5.7).
- Hepatic and Renal impairment: Maximum recommended dosage of Venlafaxine Extended-Release Tablets is 112.5 mg once daily. Switch to another venlafaxine extended-release product if doses lower than 112.5 mg are needed (2.6, 2.7).

3 DOSAGE FORMS AND STRENGTHS

- Extended-Release tablets: 112.5 mg (3).

4 CONTRAINDICATIONS

- Hypersensitivity to venlafaxine besylate, venlafaxine hydrochloride, desvenlafaxine succinate, or any excipients in Venlafaxine Extended-Release Tablets (4).
- Concomitant use of monoamine oxidase inhibitors (MAOIs) or within 14 days of discontinuing an MAOI (4, 5.2, 7.1).

5 WARNINGS AND PRECAUTIONS

- Serotonin Syndrome: Increased risk when co-administered with other serotonergic agents, but also when taken alone. If it occurs, discontinue Venlafaxine Extended-Release Tablets and serotonergic agents and initiate supportive treatment (4, 5.2, 7.1).
- Elevated Blood Pressure: Control hypertension before initiating treatment. Monitor blood pressure regularly during treatment (5.3).
- Increased Risk of Bleeding: Concomitant use of aspirin, NSAIDs, other antiplatelet drugs, warfarin, and other anticoagulants may increase risk (5.4).
- Angle Closure Glaucoma: Angle closure glaucoma has occurred in patients with untreated anatomically narrow angles treated with antidepressants (5.5).
- Activation of Mania/Hypomania: Screen patients for bipolar disorder (2.4, 5.6).
- Discontinuation Syndrome: Taper dose and monitor for discontinuation symptoms (5.7).
- Seizure: Can occur. Use with caution in patients with seizure disorder (5.8).
- Hyponatremia: Can occur in association with SIADH (5.9).
- Interstitial Lung Disease and Eosinophilic Pneumonia: Can occur (5.12).
- Sexual Dysfunction: Venlafaxine Extended-Release Tablets may cause symptoms of sexual dysfunction (5.13).

6 ADVERSE REACTIONS

Most common adverse reactions (incidence ≥5% and at least twice the rate of placebo): nausea, somnolence, dry mouth, sweating, abnormal ejaculation, anorexia, constipation, impotence (men), and libido decreased (6.1).

To report SUSPECTED ADVERSE REACTIONS, contact Almatica Pharma LLC at 1-877-447-7979 or FDA at 1-800-FDA-1088 or www.fda.gov/medwatch.

7 DRUG INTERACTIONS

- Alcohol: Increases the release rate of Venlafaxine Extended-Release Tablets. Avoid concomitant use (7.1).

8 USE IN SPECIFIC POPULATIONS

- Pregnancy: Third trimester use may increase risk for symptoms of poor neonatal adaptation (respiratory distress, temperature instability, feeding difficulty, hypotonia, tremor, irritability) in the neonate (8.1).

FULL PRESCRIBING INFORMATION

WARNING: SUICIDAL THOUGHTS AND BEHAVIORS

Antidepressants increased the risk of suicidal thoughts and behavior in pediatric and young adult patients in short-term studies. Closely monitor all antidepressant-treated patients for clinical worsening, and emergence of suicidal thoughts and behaviors [see Warnings and Precautions (5.1)].

Venlafaxine Extended-Release Tablets are not approved for use in pediatric patients [see Use in Specific Populations (8.4)].

1 INDICATIONS AND USAGE

Venlafaxine Extended-Release Tablets are indicated in adults for the treatment of:

- Major depressive disorder (MDD)
- Generalized Anxiety Disorder (GAD)

2 DOSAGE AND ADMINISTRATION

2.1 Important Dosing and Administration Information

Do not initiate venlafaxine treatment, titrate by doses less than 112.5 mg, or taper treatment with Venlafaxine Extended-Release Tablets, as dosing is not possible in these scenarios because Venlafaxine Extended-Release Tablets are only available in a 112.5 mg strength. Use another venlafaxine extended-release product for dosage initiation, titration, administration of dosages below 112.5 mg once daily, and to taper during discontinuation [see Dosage and Administration (2.6, 2.7, 2.8)]. Refer to the Prescribing Information of other venlafaxine extended-release products for the recommended dosage of those products in these dosing scenarios.

Venlafaxine Extended-Release Tablets can be initiated in patients who have received at least 75 mg per day of another venlafaxine extended-release product for at least 4 days [see Dosage and Administration (2.2, 2.3)].

Administer Venlafaxine Extended-Release Tablets as once daily with food, either in the morning or in the evening at approximately the same time each day [see Clinical Pharmacology (12.3)]. Swallow tablets whole with fluid. Do not divide, crush, chew, or place in water.

2.2 Recommended Dosage for the Treatment of Major Depressive Disorder

Initiate Venlafaxine Extended-Release Tablets at a dosage of 112.5 mg once daily in patients who have received at least 75 mg per day of another venlafaxine extended-release product for at least 4 days [see Dosage and Administration (2.1)].

Patients not responding to their current venlafaxine dosage may benefit from dose increases to a maximum of 225 mg per day. Increase the dosage in increments of up to 75 mg per day, as needed, using another venlafaxine extended-release product at intervals of 4 days or more.

2.3 Recommended Dosage for the Treatment of Generalized Anxiety Disorder

Initiate Venlafaxine Extended-Release Tablets at a dosage of 112.5 mg once daily in patients who have received at least 75 mg per day of another venlafaxine extended-release product for at least 4 days [see Dosage and Administration (2.1)].

Patients not responding to their current venlafaxine dosage may benefit from dose increases to a maximum of 225 mg per day. Increase the dosage in increments of up to 75 mg per day, as needed, using another venlafaxine extended-release product at intervals of 4 days or more.

2.4 Screen for Bipolar Disorder Prior to Starting Venlafaxine Extended-Release Tablets

Prior to initiating treatment with Venlafaxine Extended-Release Tablets, screen patients for a personal or family history of bipolar disorder, mania, or hypomania [see Warnings and Precautions (5.6)].

2.5 Switching Patients from Venlafaxine Tablets (Immediate-Release Formulation)

Patients who are currently receiving venlafaxine tablets (immediate-release formulation) may be switched to Venlafaxine Extended-Release Tablets at the nearest equivalent dose (mg per day) if the total daily dosage is either 112.5 mg or 225 mg once daily.

2.6 Dosage Recommendations in Patients with Hepatic Impairment

Reduce the total daily dose of venlafaxine by 50% in patients with mild (Child-Pugh Class A) to moderate (Child-Pugh Class B) hepatic impairment. In patients with severe hepatic impairment (Child-Pugh Class C) or hepatic cirrhosis, it may be necessary to reduce the dose by 50% or more [see Use in Specific Populations (8.6)].

The maximum recommended dosage of Venlafaxine Extended-Release Tablets in patients with hepatic impairment is 112.5 mg once daily. If the total daily dosage of venlafaxine is less than 112.5 mg per day, use another venlafaxine extended-release product [see Dosage and Administration (2.1)].

2.7 Dosage Recommendations in Patients with Renal Impairment

Reduce the total daily dose of venlafaxine by 25% to 50% in patients with mild (CLcr = 60-89 mL/min) or moderate (CLcr = 30-59 mL/min) renal impairment. In patients undergoing hemodialysis or with severe renal impairment (CLcr < 30 mL/min), the total daily dose should be reduced by 50% or more [see Use in Specific Populations (8.7)].

The maximum recommended dosage of Venlafaxine Extended-Release Tablets in patients with renal impairment is 112.5 mg once daily. If the total daily dosage of venlafaxine is less than 112.5 mg per day, use another venlafaxine extended-release product [see Dosage and Administration (2.1)].

2.8 Discontinuing Treatment with Venlafaxine Extended-Release Tablets

A gradual reduction in the dose, rather than abrupt cessation, is recommended whenever possible when discontinuing Venlafaxine Extended-Release Tablets. In clinical studies with venlafaxine extended-release capsules, tapering was achieved by reducing the daily dosage by 75 mg at one-week intervals.

Given that dosage strengths of Venlafaxine Extended-Release Tablets are not available below 112.5 mg, use another venlafaxine extended-release product for discontinuation [see Dosage and Administration (2.1)]. Individualization of tapering may be necessary. In some patients, discontinuation may need to occur over a period of several months [see Warnings and Precautions (5.7)].

2.9 Switching Patients to or from a Monoamine Oxidase Inhibitor (MAOI) Antidepressant

At least 14 days must elapse between discontinuation of an MAOI (intended to treat psychiatric disorders) and initiation of therapy with Venlafaxine Extended-Release Tablets. In addition, at least 7 days should be allowed after stopping Venlafaxine Extended-Release Tablets before starting an MAOI intended to treat psychiatric disorders [see Contraindications (4), Warnings and Precautions (5.2), and Drug Interactions (7.1)].

3 DOSAGE FORMS AND STRENGTHS

Extended-release tablets: 112.5 mg, white, round, biconvex tablet, with “ALM” over “632” printed in black ink on one side, and plain on the other side.

4 CONTRAINDICATIONS

Venlafaxine Extended-Release Tablets are contraindicated in patients:

- with known hypersensitivity to venlafaxine besylate, venlafaxine hydrochloride, desvenlafaxine succinate or to any excipients in Venlafaxine Extended-Release Tablets [see Adverse Reactions (6.2)].
- taking, or within 14 days of stopping, MAOIs (including the MAOIs linezolid and intravenous methylene blue) because of increased risk of serotonin syndrome [see Dosage and Administration (2.9), Warnings and Precautions (5.2), Drug Interactions (7.1)].

5 WARNINGS AND PRECAUTIONS

5.1 Suicidal Thoughts and Behaviors in Adolescents and Young Adults

In pooled analyses of placebo-controlled trials of antidepressant drugs (SSRIs and other antidepressant classes) that included approximately 77,000 adult patients and 4,500 pediatric patients, the incidence of suicidal thoughts and behaviors in antidepressant-treated patients age 24 years and younger was greater than in placebo-treated patients. There was considerable variation in risk of suicidal thoughts and behaviors among drugs, but there was an increased risk identified in young patients for most drugs studied. There were differences in absolute risk of suicidal thoughts and behaviors across the different indications, with the highest incidence in patients with MDD. The drug-placebo differences in the number of cases of suicidal thoughts and behaviors per 1,000 patients treated are provided in Table 1.

Table 1: Risk Differences of the Number of Patients of Suicidal Thoughts and Behaviors in the Pooled Placebo-Controlled Trials of Antidepressants in Pediatric* and Adult Patients
Age Range | Drug-Placebo Difference in Number of Patients of Suicidal Thoughts and Behaviors per 1,000 Patients Treated
 | Increases Compared to Placebo
< 18 years old | 14 additional patients
18–24 years old | 5 additional patients
 | Decreases Compared to Placebo
25–64 years old | 1 fewer patient
≥ 65 years old | 6 fewer patients
*Venlafaxine Extended-Release Tablets are not approved for use in pediatric patients.

It is unknown whether the risk of suicidal thoughts and behaviors in children, adolescents, and young adults extends to longer-term use, i.e., beyond four months. However, there is substantial evidence from placebo-controlled maintenance trials in adults with MDD that antidepressants delay the recurrence of depression and that depression itself is a risk factor for suicidal thoughts and behaviors.

Monitor all antidepressant-treated patients for any indication for clinical worsening and emergence of suicidal thoughts and behaviors, especially during the initial few months of drug therapy, and at times of dosage changes. Counsel family members or caregivers of patients to monitor for changes in behavior and to alert the healthcare provider. Consider changing the therapeutic regimen, including possibly discontinuing Venlafaxine Extended-Release Tablets, in patients whose depression is persistently worse, or who are experiencing emergent suicidal thoughts or behaviors.

5.2 Serotonin Syndrome

Serotonin-norepinephrine reuptake inhibitors (SNRIs), including Venlafaxine Extended-Release Tablets, can precipitate serotonin syndrome, a potentially life-threatening condition. The risk is increased with concomitant use of other serotonergic drugs (including triptans, tricyclic antidepressants, fentanyl, lithium, tramadol, meperidine, methadone, tryptophan, buspirone, amphetamines, and St. John’s Wort) and with drugs that impair metabolism of serotonin, i.e., MAOIs [see Contraindications (4), Drug Interactions (7.1)]. Serotonin syndrome can also occur when these drugs are used alone.

Serotonin syndrome signs and symptoms may include mental status changes (e.g., agitation, hallucinations, delirium, coma), autonomic instability (e.g., tachycardia, labile blood pressure, dizziness, diaphoresis, flushing, hyperthermia), neuromuscular symptoms (e.g., tremor, rigidity, myoclonus, hyperreflexia, incoordination), seizures, and gastrointestinal symptoms (e.g., nausea, vomiting, diarrhea).

The concomitant use of Venlafaxine Extended-Release Tablets with MAOIs is contraindicated. In addition, do not initiate Venlafaxine Extended-Release Tablets in a patient being treated with MAOIs such as linezolid or intravenous methylene blue. No reports involved the administration of methylene blue by other routes (such as oral tablets or local tissue injection). If it is necessary to initiate treatment with an MAOI such as linezolid or intravenous methylene blue in a patient taking Venlafaxine Extended-Release Tablets, discontinue Venlafaxine Extended-Release Tablets before initiating treatment with the MAOI [see Dosage and Administration (2.9), Contraindications (4), Drug Interactions (7.1)].

Monitor all patients taking Venlafaxine Extended-Release Tablets for the emergence of serotonin syndrome. Discontinue treatment with Venlafaxine Extended-Release Tablets and any concomitant serotonergic agents immediately if the above symptoms occur, and initiate supportive symptomatic treatment. If concomitant use of Venlafaxine Extended-Release Tablets with other serotonergic drugs is clinically warranted, inform patients of the increased risk for serotonin syndrome and monitor for symptoms.

5.3 Elevated Blood Pressure

In controlled trials, there were dose-related increases in systolic and diastolic blood pressure, as well as cases of sustained hypertension [see Adverse Reactions (6.1)].

Monitor blood pressure before initiating treatment with Venlafaxine Extended-Release Tablets and regularly during treatment. Control pre-existing hypertension before initiating treatment with Venlafaxine Extended-Release Tablets. Use caution in treating patients with pre-existing hypertension or cardiovascular or cerebrovascular conditions that might be compromised by increases in blood pressure. Sustained blood pressure elevation can lead to adverse outcomes. Cases of elevated blood pressure requiring immediate treatment have been reported with venlafaxine extended-release capsules. Consider dose reduction or discontinuation of treatment for patients who experience a sustained increase in blood pressure.

Across all clinical studies with venlafaxine, 1.4% of patients in the venlafaxine extended-release capsules treated groups experienced a ≥15 mm Hg increase in supine diastolic blood pressure (SDBP) ≥ 105 mm Hg, compared to 0.9% of patients in the placebo groups. Similarly, 1% of patients in the venlafaxine extended-release capsules treated groups experienced a ≥ 20 mm Hg increase in supine systolic blood pressure (SSBP) with blood pressure ≥ 180 mm Hg, compared to 0.3% of patients in the placebo groups [see Adverse Reactions (6.1)]. Treatment with venlafaxine extended-release capsules was associated with sustained hypertension (defined as SDBP ≥ 90 mm Hg and ≥ 10 mm Hg above baseline for three consecutive on-therapy visits) [see Adverse Reactions (6.1)]. An insufficient number of patients received mean doses of venlafaxine extended-release capsules over 300 mg per day in clinical studies to fully evaluate the incidence of sustained increases in blood pressure at these higher doses.

5.4 Increased Risk of Bleeding

Drugs that interfere with serotonin reuptake inhibition, including Venlafaxine Extended-Release Tablets, may increase the risk of bleeding events, ranging from ecchymoses, hematomas, epistaxis, petechiae, and gastrointestinal hemorrhage to life-threatening hemorrhage. Concomitant use of aspirin, Nonsteroidal Anti-Inflammatory Drugs (NSAIDs), warfarin, and other anti-coagulants or other drugs known to affect platelet function may add to this risk. Case reports and epidemiological studies (case-control and cohort design) have demonstrated an association between use of drugs that interfere with serotonin reuptake and the occurrence of gastrointestinal bleeding. Based on data from the published observational studies, exposure to SNRIs, particularly in the month before delivery, has been associated with a less than 2-fold increase in the risk of postpartum hemorrhage [see Use in Specific Populations (8.1)].

Inform patients about the increased risk of bleeding associated with the concomitant use of Venlafaxine Extended-Release Tablets and antiplatelet agents or anticoagulants. For patients taking warfarin, carefully monitor coagulation indices when initiating, titrating, or discontinuing Venlafaxine Extended-Release Tablets.

5.5 Angle-Closure Glaucoma

The pupillary dilation that occurs following use of many antidepressant drugs, including Venlafaxine Extended-Release Tablets, may trigger an angle closure attack in a patient with anatomically narrow angles who does not have a patent iridectomy. Avoid use of antidepressants, including Venlafaxine Extended-Release Tablets, in patients with untreated anatomically narrow angles.

5.6 Activation of Mania/Hypomania

In patients with bipolar disorder, treating a depressive episode with Venlafaxine Extended-Release Tablets or another antidepressant may precipitate a mixed/manic episode. Mania or hypomania was reported in venlafaxine extended-release capsules treated patients in the premarketing studies in MDD (see Table 2). Prior to initiating treatment with Venlafaxine Extended-Release Tablets, screen for any personal or family history of bipolar, mania, or hypomania.

Table 2: Incidence (%) of Mania or Hypomania Reported in Venlafaxine Extended-Release Capsules Treated Patients in the Premarketing Studies
Indication | Venlafaxine Extended-Release Capsules | Placebo
MDD | 0.3 | 0.0
GAD | 0.0 | 0.2

5.7 Discontinuation Syndrome

Discontinuation symptoms have been systematically evaluated in patients taking venlafaxine, including prospective analyses of clinical studies in GAD and retrospective surveys of studies in MDD. Abrupt discontinuation or dose reduction of venlafaxine at various doses has been found to be associated with the appearance of new symptoms, the frequency of which increased with increased dose level and with longer duration of treatment. Reported symptoms include agitation, anorexia, anxiety, confusion, impaired coordination and balance, diarrhea, dizziness, dry mouth, dysphoric mood, fasciculation, fatigue, flu-like symptoms, headaches, hypomania, insomnia, nausea, nervousness, nightmares, sensory disturbances (including shock-like electrical sensations), somnolence, sweating, tremor, vertigo, and vomiting.

There have been postmarketing reports of serious discontinuation symptoms which can be protracted and severe. Completed suicide, suicidal thoughts, aggression and violent behavior have been observed in patients during reduction in venlafaxine extended-release capsules dosage, including during discontinuation. Other postmarketing reports describe visual changes (such as blurred vision or trouble focusing) and increased blood pressure after stopping or reducing the dose of venlafaxine extended-release capsules. During marketing of venlafaxine extended-release capsules, other SNRIs, and SSRIs, there have been reports of adverse events occurring upon discontinuation of these drugs, particularly when abrupt, including the following: irritability, lethargy, emotional lability, tinnitus, and seizures.

Patients should be monitored for these symptoms when discontinuing treatment with Venlafaxine Extended-Release Tablets. A gradual reduction in the dose, rather than abrupt cessation, is recommended. If intolerable symptoms occur following a decrease in the dose or upon discontinuation of treatment, then resuming the previously prescribed dose may be considered. Subsequently, the healthcare provider may continue decreasing the dose, but at a more gradual rate. In some patients, discontinuation may need to occur over a period of several months [see Dosage and Administration (2.8)]. Given that dosage strengths of Venlafaxine Extended-Release Tablets are not available below 112.5 mg, use another venlafaxine extended-release product for discontinuation [see Dosage and Administration (2.1)].

5.8 Seizures

Cases of seizures have been reported with venlafaxine therapy. Venlafaxine Extended-Release Tablets has not been systematically evaluated in patients with seizure disorder. Venlafaxine Extended-Release Tablets should be prescribed with caution in patients with a history of seizures and should be discontinued in any patient who develops seizures.

5.9 Hyponatremia

Hyponatremia can occur as a result of treatment with SNRIs, including Venlafaxine Extended-Release Tablets In many cases, the hyponatremia appears to be the result of the Syndrome of Inappropriate Antidiuretic Hormone (SIADH) secretion. Cases with serum sodium lower than 110 mmol/L have been reported. Elderly patients may be at greater risk of developing hyponatremia with SSRIs and SNRIs. Also, patients taking diuretics, or those who are otherwise volume-depleted, may be at greater risk [see Use in Specific Populations (8.5) and Clinical Pharmacology (12.3)]. Consider discontinuation of Venlafaxine Extended-Release Tablets in patients with symptomatic hyponatremia, and institute appropriate medical intervention.

Signs and symptoms of hyponatremia include headache, difficulty concentrating, memory impairment, confusion, weakness, and unsteadiness, which may lead to falls. Signs and symptoms associated with more severe and/or acute cases have included hallucination, syncope, seizure, coma, respiratory arrest, and death.

5.10 Weight and Height Changes in Pediatric Patients

Weight Changes

The average change in body weight and incidence of weight loss (percentage of patients who lost 3.5% or more) in the placebo-controlled pediatric studies in MDD and GAD with venlafaxine extended-release capsules are shown in Tables 3 and 4.

Venlafaxine Extended-Release Tablets are not approved for use in pediatric patients [see Use in Specific Populations (8.4)].

Table 3: Average Change in Body Weight (kg) From Beginning of Treatment in Pediatric Patientsa in Double-blind, Placebo-controlled Studies of Venlafaxine Extended-Release Capsules
Indication (Study Duration) | Venlafaxine Extended-Release Capsules | Placebo
MDD and GAD (4 pooled studies, 8 weeks) | -0.45 (n = 333) | +0.77 (n = 333)
aVenlafaxine Extended-Release Tablets are not approved for use in pediatric patients.

Table 4: Incidence (%) of Pediatric Patientsa Experiencing Weight Loss (3.5% or more) in Double-blind, Placebo-controlled Studies of Venlafaxine Extended-Release Capsules
Indication (Study Duration) | Venlafaxine Extended-Release Capsules | Placebo
MDD and GAD (4 pooled studies, 8 weeks) | 18b (n = 333) | 3.6 (n = 333)
a Venlafaxine Extended-Release Tablets are not approved for use in pediatric patients.
b p < 0.001 versus placebo

Weight loss was not limited to patients with anorexia [see Warnings and Precautions (5.11)].

The risks associated with longer term use of venlafaxine extended-release capsules were assessed in an open-label MDD study of pediatric patients 6 years to 17 years old who received venlafaxine extended-release capsules for up to six months. The pediatric patients 6 years to 17 years old in the study had increases in weight that were less than expected, based on data from age- and sex-matched peers. The difference between observed weight gain and expected weight gain was larger for pediatric patients 6 years to < 12 years old than for pediatric patients ≥ 12 years old.

Height Changes

Table 5 shows the average height increase in pediatric patients in the short-term, placebo-controlled MDD and GAD studies with venlafaxine extended-release capsules. The differences in height increases in GAD and MDD studies were most notable in patients younger than twelve.

Venlafaxine Extended-Release Tablets are not approved for use in pediatric patients [see Use in Specific Populations (8.4)].

Table 5: Average Height Increases (cm) in Pediatric Patientsa in Placebo-controlled Studies of Venlafaxine Extended-Release Capsules
Indication (Study Duration) | Venlafaxine Extended-Release Capsules | Placebo
MDD (8 weeks) | 0.8 (n = 146) | 0.7 (n = 147)
GAD (8 weeks) | 0.3b (n = 122) | 1.0 (n = 132)
a Venlafaxine Extended-Release Tablets are not approved for use in pediatric patients.
b p = 0.041

In the six-month, open-label MDD study with venlafaxine extended-release capsules, pediatric patients 6 years to 17 years old had height increases that were less than expected, based on data from age- and sex-matched peers. The difference between observed and expected growth rates was larger for pediatric patients 6 years to < 12 years old than for pediatric patients ≥ 12 years old [see Use in Specific Populations (8.4)].

5.11 Appetite Changes in Pediatric Patients

Decreased appetite (reported as anorexia) was more commonly observed in venlafaxine extended-release capsule-treated pediatric patients 6 years to 17 years old versus placebo-treated patients in the premarketing evaluation of venlafaxine extended-release capsules for MDD and GAD (see Table 6).

Venlafaxine Extended-Release Tablets are not approved for use in pediatric patients [see Use in Specific Populations (8.4)].

Table 6: Incidence (%) of Decreased Appetite and Associated Discontinuation Ratesa (%) in Pediatric Patientsb in Placebo-controlled Studies of Venlafaxine Extended-Release Capsules
Indication (Study Duration) | Venlafaxine Extended-Release Capsules Incidence | Discontinuation | Placebo Incidence
MDD and GAD (pooled, 8 weeks) | 10 | 0.0 | 3
a The discontinuation rates for weight loss were 0.7% for patients receiving either venlafaxine extended-release capsules or placebo.
b Venlafaxine Extended-Release Tablets are not approved for use in pediatric patients.

5.12 Interstitial Lung Disease and Eosinophilic Pneumonia

Interstitial lung disease and eosinophilic pneumonia associated with venlafaxine therapy have been rarely reported. The possibility of these events should be considered in Venlafaxine Extended-Release Tablets patients who present with progressive dyspnea, cough or chest discomfort. Such patients should undergo a prompt medical evaluation, and discontinuation of Venlafaxine Extended-Release Tablets should be considered.

5.13 Sexual Dysfunction

Use of SNRIs, including Venlafaxine Extended-Release Tablets, may cause symptoms of sexual dysfunction [see Adverse Reactions (6.1)]. In male patients, SNRI use may result in ejaculatory delay or failure, decreased libido, and erectile dysfunction. In female patients, SNRI use may result in decreased libido and delayed or absent orgasm.

It is important for prescribers to inquire about sexual function prior to initiation of Venlafaxine Extended-Release Tablets and to inquire specifically about changes in sexual function during treatment, because sexual function may not be spontaneously reported. When evaluating changes in sexual function, obtaining a detailed history (including timing of symptom onset) is important because sexual symptoms may have other causes, including the underlying psychiatric disorder. Discuss potential management strategies to support patients in making informed decisions about treatment.

6 ADVERSE REACTIONS

The following adverse reactions are discussed in more detail in other sections of the labeling:

- Hypersensitivity [see Contraindications (4)]
- Suicidal Thoughts and Behaviors in Adolescents and Young Adults [see Warnings and Precautions (5.1)]
- Serotonin Syndrome [see Warnings and Precautions (5.2)]
- Elevated Blood Pressure [see Warnings and Precautions (5.3)]
- Increased Risk of Bleeding [see Warnings and Precautions (5.4)]
- Angle-Closure Glaucoma [see Warnings and Precautions (5.5)]
- Activation of Mania/Hypomania [see Warnings and Precautions (5.6)]
- Discontinuation Syndrome [see Warnings and Precautions (5.7)]
- Seizures [see Warnings and Precautions (5.8)]
- Hyponatremia [see Warnings and Precautions (5.9)]
- Weight and Height Changes in Pediatric Patients [see Warnings and Precautions (5.10)]
- Appetite Changes in Pediatric Patients [see Warnings and Precautions (5.11)]
- Interstitial Lung Disease and Eosinophilic Pneumonia [see Warnings and Precautions (5.12)]
- Sexual Dysfunction [see Warnings and Precautions (5.13)]

6.1 Clinical Studies Experience

Because clinical studies are conducted under widely varying conditions, adverse reaction rates observed in the clinical studies of a drug cannot be directly compared to rates in the clinical studies of another drug and may not reflect the rates observed in practice.

The safety of Venlafaxine Extended-Release Tablets for the treatment of MDD and GAD is based on adequate and well controlled studies of venlafaxine extended-release capsules. Below is a display of adverse reactions of venlafaxine extended-release capsules from those adequate and well-controlled studies in MDD, GAD, and other indications.

Most Common Adverse Reactions

The most commonly observed adverse reactions in the clinical study database in venlafaxine extended-release capsules treated patients in MDD, GAD, and other indications (incidence ≥ 5% and at least twice the rate of placebo) were: nausea (30.0%), somnolence (15.3%), dry mouth (14.8%), sweating (11.4%), abnormal ejaculation (9.9%), anorexia (9.8%), constipation (9.3%), impotence (5.3%) and decreased libido (5.1%).

Adverse Reactions Reported as Reasons for Discontinuation of Treatment

Combined across short-term, placebo-controlled premarketing studies for MDD, GAD, and other indications, 12% of the 3,558 patients who received venlafaxine extended-release capsules within a dosage range of 37.5 mg to 225 mg discontinued treatment due to an adverse reaction, compared with 4% of the 2,197 placebo-treated patients in those studies [Venlafaxine Extended-Release Tablets are only available as 112.5 mg dosage strength].

The most common adverse reactions leading to discontinuation in ≥ 1% of the venlafaxine extended-release capsules treated patients in the short-term studies (up to 12 weeks) in MDD, GAD, and other indications are shown in Table 7.

Table 7: Adverse Reactions Leading to Discontinuation in Venlafaxine Extended-Release Capsule Placebo-controlled Clinical Studies (up to 12 Weeks Duration)
Body System; Adverse Reaction | Venlafaxine; Extended-Release Capsules; n = 3,558 | Placebo; n = 2,197
Body as a whole
Asthenia | 1.7 | 0.5
Headache | 1.5 | 0.8
Digestive system
Nausea | 4.3 | 0.4
Nervous system
Dizziness | 2.2 | 0.8
Insomnia | 2.1 | 0.6
Somnolence | 1.7 | 0.3
Skin and appendages | 1.5 | 0.6
Sweating | 1.0 | 0.2

Common Adverse Reactions in Placebo-controlled Studies

Common adverse reactions (those that occurred in ≥ 2% of venlafaxine extended-release capsules treated patients [357 MDD patients, 1,381 GAD patients, and 1,820 patients for other indications] and more frequently than placebo) in venlafaxine extended-release capsules treated patients in short-term, placebo-controlled, fixed- and flexible-dose clinical studies within a dosage range of doses 37.5 mg to 225 mg per day are shown in Table 8 [Venlafaxine Extended-Release Tablets are only available as 112.5 mg dosage strength].

The adverse reaction profile did not differ substantially between the different patient populations.

Table 8: Percentage of Patients Reporting Adverse Reactions (≥ 2% and > placebo) in Placebo-controlled Studies of Venlafaxine Extended-Release Capsules (up to 12 Weeks Duration) in MDD, GAD, and Other Indications
Body System; Adverse Reaction | Venlafaxine; Extended-Release Capsules; n = 3,558 | Placebo; n = 2,197
Body as a whole
Asthenia | 12.6 | 7.8
Cardiovascular system
Hypertension | 3.4 | 2.6
Palpitation | 2.2 | 2.0
Vasodilatation | 3.7 | 1.9
Digestive system
Anorexia | 9.8 | 2.6
Constipation | 9.3 | 3.4
Diarrhea | 7.7 | 7.2
Dry mouth | 14.8 | 5.3
Nausea | 30.0 | 11.8
Vomiting | 4.3 | 2.7
Nervous system
Abnormal dreams | 2.9 | 1.4
Dizziness | 15.8 | 9.5
Insomnia | 17.8 | 9.5
Libido decreased | 5.1 | 1.6
Nervousness | 7.1 | 5.0
Paresthesia | 2.4 | 1.4
Somnolence | 15.3 | 7.5
Tremor | 4.7 | 1.6
Respiratory system
Yawn | 3.7 | 0.2
Skin and appendages
Sweating (including night sweats) | 11.4 | 2.9
Special senses
Abnormal vision | 4.2 | 1.6
Urogenital system
Abnormal ejaculation/orgasm (men)a | 9.9 | 0.5
Anorgasmia (men)a | 3.6 | 0.1
Anorgasmia (women)b | 2.0 | 0.2
Impotence (men)a | 5.3 | 1.0
a Percentages based on the number of men (venlafaxine extended-release capsules, n = 1,440; placebo, n = 923)
b Percentages based on the number of women (venlafaxine extended-release capsules, n = 2,118; placebo, n = 1,274)

Other Adverse Reactions Observed in Clinical Studies

Body as a whole – Photosensitivity reaction, chills

Cardiovascular system – Postural hypotension, syncope, hypotension, tachycardia

Digestive system – Gastrointestinal hemorrhage [see Warnings and Precautions (5.4)], bruxism

Hemic/Lymphatic system – Ecchymosis [see Warnings and Precautions (5.4)]

Metabolic/Nutritional – Hypercholesterolemia, weight gain [see Warnings and Precautions (5.10)], weight loss [see Warnings and Precautions (5.10)]

Nervous system – Seizures [see Warnings and Precautions (5.8)], manic reaction [see Warnings and Precautions (5.6)], agitation, confusion, akathisia, hallucinations, hypertonia, myoclonus, depersonalization, apathy

Skin and appendages – Urticaria, pruritus, rash, alopecia

Special senses – Mydriasis, abnormality of accommodation, tinnitus, taste perversion

Urogenital system – Urinary retention, urination impaired, urinary incontinence, urinary frequency increased, menstrual disorders associated with increased bleeding or increased irregular bleeding (e.g., menorrhagia, metrorrhagia)

Vital Sign Changes

In placebo-controlled premarketing studies, there were increases in mean blood pressure (see Table 9). A dose-related increase in mean supine systolic and diastolic blood pressure was evident in patients treated with venlafaxine extended-release capsules. Across all clinical studies in MDD, GAD, and other indications, 1.4% of patients in the venlafaxine extended-release capsules groups experienced an increase in SDBP of ≥15 mm Hg along with a blood pressure ≥ 105 mm Hg, compared to 0.9% of patients in the placebo groups. Similarly, 1% of patients in the venlafaxine extended-release capsules groups experienced an increase in SSBP of ≥ 20 mm Hg with a blood pressure ≥ 180 mm Hg, compared to 0.3% of patients in the placebo groups.

Table 9: Final On-therapy Mean Changes from Baseline in Supine Systolic (SSBP) and Diastolic (SDBP) Blood Pressure (mm Hg) in Placebo-controlled Studies
 | Venlafaxine Extended-Release Capsules |  |  |  | Placebo
Indication | ≤ 75 mg per daya |  | > 75 mg per daya,b
(Duration) | SSBP | SDBP | SSBP | SDBP | SSBP | SDBP
MDD
(8–12 weeks) | -0.28 | 0.37 | 2.93 | 3.56 | -1.08 | -0.10
GAD
(8 weeks) | -0.28 | 0.02 | 2.40 | 1.68 | -1.26 | -0.92
(6 months) | 1.27 | -0.69 | 2.06 | 1.28 | -1.29 | -0.74
a Venlafaxine Extended-Release Tablets are only available as 112.5 mg dosage strength.
b Maximum recommended dosage for Venlafaxine Extended-Release Tablets is 225 mg once daily.

Venlafaxine extended-release capsules treatment was associated with sustained hypertension (defined as Supine Diastolic Blood Pressure [SDBP] ≥ 90 mm Hg and ≥ 10 mm Hg above baseline for three consecutive on-therapy visits (see Table 10).

Table 10: Sustained Elevations in SDBP in Venlafaxine Extended-Release Capsules Premarketing Studies
Indication | Dose Range; (mg per day)a | Incidence; (%)
MDD | 75a to 375b | 19/705 (3)
GAD | 37.5a to 225 | 5/1011 (0.5)
a Venlafaxine Extended-Release Tablets are only available as 112.5 mg dosage strength.
b Maximum recommended dosage for Venlafaxine Extended-Release Tablets is 225 mg once daily.

Venlafaxine extended-release capsules was associated with mean increases in pulse rate compared with placebo in premarketing placebo-controlled studies (see Table 11) [see Warnings and Precautions (5.3, 5.4)].

Table 11: Approximate Mean Final On-therapy Increase in Pulse Rate (beats/min) in Venlafaxine Extended-Release Capsules Premarketing Placebo-controlled Studies (up to 12 Weeks Duration)
Indication; (Duration) | Venlafaxine; Extended-Release Capsules | Placebo
MDD; (12 weeks) | 2 | 1
GAD; (8 weeks) | 2 | < 1

Laboratory Changes

Serum Cholesterol

Venlafaxine extended-release capsules was associated with mean final increases in serum cholesterol concentrations compared with mean final decreases for placebo in premarketing MDD and GAD clinical studies (Table 12).

Table 12: Mean Final On-therapy Changes in Cholesterol Concentrations (mg/dL) in Venlafaxine Extended-Release Capsules Premarketing Studies
Indication; (Duration) | Venlafaxine; Extended-Release Capsules |  | Placebo
MDD
(12 weeks) |  | +1.5 | -7.4
GAD
(8 weeks) |  | +1.0 | -4.9
(6 months) |  | +2.3 | -7.7

Venlafaxine extended-release capsules treatment for up to 12 weeks in premarketing placebo-controlled trials for major depressive disorder was associated with a mean final on-therapy increase in serum cholesterol concentration of approximately 1.5 mg/dL compared with a mean final decrease of 7.4 mg/dL for placebo. Venlafaxine extended-release capsules treatment for up to 8 weeks and up to 6 months in premarketing placebo-controlled GAD trials was associated with mean final on-therapy increases in serum cholesterol concentration of approximately 1.0 mg/dL and 2.3 mg/dL, respectively while placebo subjects experienced mean final decreases of 4.9 mg/dL and 7.7 mg/dL, respectively.

6.2 Postmarketing Experience

The following adverse reactions have been identified during post approval use of venlafaxine extended-release capsules. Because these reactions are reported voluntarily from a population of uncertain size, it is not always possible to reliably estimate their frequency or establish a causal relationship to drug exposure.

Body as a whole – Anaphylaxis, angioedema

Cardiovascular system – QT prolongation, ventricular fibrillation, ventricular tachycardia (including torsade de pointes), takotsubo cardiomyopathy

Digestive system – Pancreatitis

Hemic/Lymphatic system – Mucous membrane bleeding [see Warnings and Precautions (5.4)], blood dyscrasias (including agranulocytosis, aplastic anemia, neutropenia and pancytopenia), prolonged bleeding time, thrombocytopenia

Metabolic/Nutritional – Hyponatremia [see Warnings and Precautions (5.9)], Syndrome of Inappropriate Antidiuretic Hormone (SIADH) secretion [see Warnings and Precautions (5.9)], abnormal liver function tests, hepatitis, prolactin increased

Musculoskeletal – Rhabdomyolysis

Nervous system – Neuroleptic Malignant Syndrome (NMS) [see Warnings and Precautions (5.2)], serotonergic syndrome [see Warnings and Precautions (5.2)], delirium, extrapyramidal reactions (including dystonia and dyskinesia), impaired coordination and balance, tardive dyskinesia

Respiratory, thoracic and mediastinal disorders – Anosmia, dyspnea, hyposmia, interstitial lung disease, pulmonary eosinophilia [see Warnings and Precautions (5.12)]

Skin and appendages – Stevens-Johnson syndrome, toxic epidermal necrolysis, erythema multiforme

Special senses – Angle-closure glaucoma [see Warnings and Precautions (5.5)]

7 DRUG INTERACTIONS

7.1 Drugs Having Clinically Important Interactions with Venlafaxine Extended-Release Tablets

Table 13: Clinically Significant Drug Interactions with Venlafaxine Extended-Release Tablets
Monoamine Oxidase Inhibitors (MAOI)
Clinical Impact | Concomitant use of SNRIs, including Venlafaxine Extended-Release Tablets, with MAOIs increases the risk of serotonin syndrome.
Intervention | Concomitant use of Venlafaxine Extended-Release Tablets is contraindicated in patients taking MAOIs, including MAOIs such as linezolid or intravenous methylene blue [see Dosage and Administration (2.9), Contraindications (4), and Warnings and Precautions (5.2)].
Other Serotonergic Drugs
Clinical Impact | Concomitant use of Venlafaxine Extended-Release Tablets with other serotonergic drugs (including other SNRIs, SSRIs, triptans, tricyclic antidepressants, opioids, lithium, buspirone, amphetamines, tryptophan, and St. John's Wort) increases the risk of serotonin syndrome.
Intervention | Monitor for symptoms of serotonin syndrome when Venlafaxine Extended-Release Tablets is used concomitantly with other drugs that may affect the serotonergic neurotransmitter systems. If serotonin syndrome occurs, consider discontinuation of Venlafaxine Extended-Release Tablets and/or concomitant serotonergic drugs [see Dosage and Administration (2.8), Warnings and Precautions (5.2)].
Alcohol
Clinical Impact | Based on an in vitro study, alcohol increases the release rate of Venlafaxine Extended-Release Tablets [see Clinical Pharmacology (12.3)].
Intervention | Avoid concomitant use of alcohol during treatment with Venlafaxine Extended-Release Tablets.
Drugs that Interfere with Hemostasis
Clinical Impact | Concomitant use of Venlafaxine Extended-Release Tablets with an antiplatelet or anticoagulant drug may potentiate the risk of bleeding. This may be due to the effect of venlafaxine on the release of serotonin by platelets.
Intervention | Closely monitor patients receiving an antiplatelet or anticoagulant drug for bleeding when Venlafaxine Extended-Release Tablets is initiated or discontinued [see Warnings and Precautions (5.4)].
CYP3A Inhibitors
Clinical Impact | Concomitant use of Venlafaxine Extended-Release Tablets with a CYP3A inhibitor increases the Cmax and AUC of venlafaxine and O-desmethylvenlafaxine (ODV) [see Clinical Pharmacology (12.3)], which may increase the risk of toxicity of venlafaxine.
Intervention | Consider reducing the dose of Venlafaxine Extended-Release Tablets.
CYP2D6 Substrates
Clinical Impact | Concomitant use of Venlafaxine Extended-Release Tablets with a CYP2D6 substrate increases Cmax and AUC of the CYP2D6 substrate, which may increase the risk of toxicity of the CYP2D6 substrate [see Clinical Pharmacology (12.3)].
Intervention | Consider reduction in dose of concomitant CYP2D6 substrates.

7.2 Other Drug Interactions with Venlafaxine Extended-Release Tablets

Weight Loss Agents

The safety and efficacy of venlafaxine therapy in combination with weight loss agents, including phentermine, have not been established. Coadministration of Venlafaxine Extended-Release Tablets and weight loss agents is not recommended. Venlafaxine Extended-Release Tablets are not indicated for weight loss alone or in combination with other products.

Laboratory Test Interference

False-positive urine immunoassay screening tests for phencyclidine (PCP) and amphetamine have been reported in patients taking venlafaxine. This is due to lack of specificity of the screening tests. False positive test results may be expected for several days following discontinuation of venlafaxine therapy. Confirmatory tests, such as gas chromatography/mass spectrometry, will distinguish venlafaxine from PCP and amphetamine.

8 USE IN SPECIFIC POPULATIONS

8.1 Pregnancy

Pregnancy Exposure Registry

There is a pregnancy exposure registry that monitors pregnancy outcomes in women exposed to antidepressants, including Venlafaxine Extended-Release Tablets, during pregnancy. Healthcare providers are encouraged to register patients by calling the National Pregnancy Registry for Antidepressants at 1-844-405-6185 or visiting online at https://womensmentalhealth.org/research/pregnancyregistry/antidepressants.

Risk Summary

Based on data from published observational studies, exposure to SNRIs, particularly in the month before delivery, has been associated with a less than 2-fold increase in the risk of postpartum hemorrhage [see Warnings and Precautions (5.4) and Clinical Considerations].

Available data from published epidemiologic studies on venlafaxine use in pregnant women have not identified a drug-associated risk of major birth defects, miscarriage, or adverse fetal outcomes (see Data). Available data from observational studies with venlafaxine have identified a potential increased risk for preeclampsia when used during mid to late pregnancy; exposure to SNRIs near delivery may increase the risk for postpartum hemorrhage (see Clinical Considerations). There are risks associated with untreated depression in pregnancy and poor neonatal adaptation in newborns exposure to SNRIs, including Venlafaxine Extended-Release Tablets, during pregnancy (see Clinical Considerations).

In animal studies, there was no evidence of malformations or fetotoxicity following administration of venlafaxine during organogenesis at doses up to 2.5 times (rat) or 4 times (rabbit) the maximum recommended human daily dose on a mg/m^2 basis. Postnatal mortality and decreased pup weights were observed following venlafaxine administration to pregnant rats during gestation and lactation at 2.5 times (mg/m^2) the maximum human daily dose.

The estimated background risk of major birth defects and miscarriage for the indicated populations is unknown. All pregnancies have a background risk of birth defect, loss, or other adverse outcomes. In the U.S. general population, the estimated background risk of major birth defects and miscarriage in clinically recognized pregnancies is 2% to 4% and 15% to 20%, respectively.

Clinical Considerations

Disease-associated maternal and/or embryo/fetal risk

Women who discontinue antidepressants during pregnancy are more likely to experience a relapse of major depression than women who continue antidepressants. This finding is from a prospective, longitudinal study of 201 women with a history of major depression who were euthymic at the beginning of pregnancy. Consider the risk of untreated depression when discontinuing or changing treatment with antidepressant medication during pregnancy and postpartum.

Maternal Adverse Reactions

Exposure to Venlafaxine Extended-Release Tablets in mid to late pregnancy may increase the risk for preeclampsia, and exposure to Venlafaxine Extended-Release Tablets in the month before near delivery may be associated with an increased the risk for of postpartum hemorrhage [see Warnings and Precautions (5.4)].

Fetal/Neonatal Adverse Reactions

Neonates exposed to SNRIs late in the third trimester have developed complications requiring prolonged hospitalization, respiratory support, and tube feeding. Such complications can arise immediately upon delivery. Reported clinical findings have included respiratory distress, cyanosis, apnea, seizures, temperature instability, feeding difficulty, vomiting, hypoglycemia, hypotonia, hypertonia, hyperreflexia, tremors, jitteriness, irritability, and constant crying. These findings are consistent with either a direct toxic effect of SNRIs or possibly a drug discontinuation syndrome. It should be noted that, in some cases, the clinical picture is consistent with serotonin syndrome [see Warnings and Precautions (5.2)]. Monitor neonates who were exposed to Venlafaxine Extended-Release Tablets in the third trimester of pregnancy for drug discontinuation syndrome.

Data

Human Data

Published epidemiological studies of pregnant women exposed to venlafaxine have not established an increase of major birth defects, miscarriage, or other adverse developmental outcomes. Methodological limitations may both fail to identify true findings and also identify findings that are not true.

Retrospective cohort studies based on claims data have shown an association between venlafaxine use and preeclampsia, compared to depressed women who did not take an antidepressant during pregnancy. One study that assessed venlafaxine exposure in the second trimester or first half of the third trimester and preeclampsia showed an increased risk compared to unexposed depressed women (adjusted (adj) RR 1.57, 95% confidence interval [CI] 1.29-1.91). Preeclampsia was observed at venlafaxine doses equal to or greater than 75 mg per day and a duration of treatment >30 days. Another study that assessed venlafaxine exposure in gestational weeks 10-20 and preeclampsia showed an increased risk at doses equal to or greater than 150 mg per day. Available data are limited by possible outcome misclassification and possible confounding due to depression severity and other confounders.

Retrospective cohort studies based on claims data have suggested an association between venlafaxine use near the time of delivery or through delivery and postpartum hemorrhage. One study showed an increased risk for postpartum hemorrhage when venlafaxine exposure occurred through delivery, compared to unexposed depressed women (adj RR 2.24 [95% CI 1.69-2.97]). There was no increased risk in women who were exposed to venlafaxine earlier in pregnancy. Limitations of this study include possible confounding due to depression severity and other confounders. Another study showed an increased risk for postpartum hemorrhage when SNRI exposure occurred for at least 15 days in the last month of pregnancy or through delivery, compared to unexposed women (adj RR 1.64-1.76). The results of this study may be confounded by the effects of depression.

Animal Data

Venlafaxine did not cause malformations in offspring of rats or rabbits given doses up to 2.5 times (rat) or 4 times (rabbit) the maximum recommended human daily dose on a mg/m^2 basis. However, in rats, there was a decrease in pup weight, an increase in stillborn pups, and an increase in pup deaths during the first 5 days of lactation, when dosing began during pregnancy and continued until weaning. The cause of these deaths is not known. These effects occurred at 2.5 times (mg/m^2) the maximum human daily dose. The no effect dose for rat pup mortality was 0.25 times the human dose on a mg/m^2 basis.

When desvenlafaxine succinate, the major metabolite of venlafaxine, was administered orally to pregnant rats and rabbits during the period of organogenesis at doses up to 300 mg/kg/day and 75 mg/kg/day, respectively, no fetal malformations were observed. These doses were associated with a plasma exposure (AUC) 19 times (rats) and 0.5 times (rabbits) the AUC exposure at an adult human dose of 100 mg per day. However, fetal weights were decreased and skeletal ossification was delayed in rats in association with maternal toxicity at the highest dose, with an AUC exposure at the no-effect dose that is 4.5-times the AUC exposure at an adult human dose of 100 mg per day.

8.2 Lactation

Risk Summary

Data from published literature report the presence of venlafaxine and its active metabolite in human milk and have not shown adverse reactions in breastfed infants (see Data). There are no data on the effects of venlafaxine on milk production.

The developmental and health benefits of breastfeeding should be considered along with the mother’s clinical need for Venlafaxine Extended-Release Tablets and any potential adverse effects on the breastfed child from Venlafaxine Extended-Release Tablets or from the underlying maternal condition.

Data

In a lactation study conducted in 11 breastfeeding women (at a mean of 20.1 months post-partum) who were taking a mean daily dose of 194.3 mg of venlafaxine and in a lactation study conducted in 6 breastfeeding women who were taking a daily dose of 225 mg to 300 mg of venlafaxine (at a mean of 7 months post-partum), the estimated mean relative infant dose was 8.1 % and 6.4% based on the sum of venlafaxine and its major metabolite, desvenlafaxine. No adverse reactions were seen in the infants.

8.4 Pediatric Use

Safety and effectiveness of Venlafaxine Extended-Release Tablets in pediatric patients have not been established.

Two placebo-controlled trials in 766 pediatric patients with MDD and two placebo-controlled trials in 793 pediatric patients with GAD have been conducted with venlafaxine extended-release capsules, and the data were not sufficient to support use in pediatric patients.

In the studies conducted in pediatric patients ages 6 to 17 years, the occurrence of blood pressure and cholesterol increases was considered to be clinically relevant in pediatric patients and was similar to that observed in adult patients [see Warnings and Precautions (5.3), Adverse Reactions (6.1)]. The following adverse reactions were also observed in pediatric patients: abdominal pain, agitation, dyspepsia, ecchymosis, epistaxis, and myalgia.

Although no studies have been designed to primarily assess Venlafaxine Extended-Release Tablet’s impact on the growth, development, and maturation of children and adolescents, the studies that have been done suggest that venlafaxine extended-release capsules may adversely affect weight and height [see Warnings and Precautions (5.10)]. Decreased appetite and weight loss were observed in placebo-controlled studies of pediatric patients 6 to 17 years [see Warnings and Precautions (5.10, 5.11)].

In pediatric clinical studies, the adverse reaction, suicidal ideation, was observed. Antidepressants increased the risk of suicidal thoughts and behaviors in pediatric patients [see Boxed Warning, Warnings and Precautions (5.1)].

8.5 Geriatric Use

The percentage of patients in clinical studies for venlafaxine extended-release capsules for MDD and GAD who were 65 years of age or older are shown in Table 14.

Table 14: Percentage (and Number of Patients Studied) of Patients 65 Years of Age and Older by Indication*
Indication | Venlafaxine Extended-Release Capsules
MDD | 4 (14/357)
GAD | 6 (77/1,381)
* In addition, in the premarketing assessment of venlafaxine tablets, 12% (357/2,897) of patients were ≥ 65 years of age.

No overall differences in effectiveness or safety were observed between geriatric patients and younger patients, and other reported clinical experience generally has not identified differences in response between the elderly and younger patients. However, greater sensitivity of some older individuals cannot be ruled out. SSRIs and SNRIs, including Venlafaxine Extended-Release Tablets, have been associated with cases of clinically significant hyponatremia in elderly patients, who may be at greater risk for this adverse event [see Warnings and Precautions (5.9)].

The pharmacokinetics of venlafaxine and ODV are not substantially altered in the elderly [see Clinical Pharmacology (12.3)]. No dose adjustment is recommended for the elderly on the basis of age alone, although other clinical circumstances, some of which may be more common in the elderly, such as renal or hepatic impairment, may warrant a dose reduction [see Dosage and Administration (2.6, 2.7)].

8.6 Hepatic Impairment

Dosage reduction is recommended in patients with mild (Child-Pugh Class A), moderate (Child-Pugh Class B), and severe (Child-Pugh Class C) hepatic impairment or hepatic cirrhosis [see Dosage and Administration (2.6) and Clinical Pharmacology (12.3)].

8.7 Renal Impairment

Dosage reduction is recommended in patients with mild (CLcr = 60-89 mL/min) or moderate (CLcr = 30-59 mL/min) renal impairment, and in patients undergoing hemodialysis or with severe renal impairment (CLcr < 30 mL/min) [see Dosage and Administration (2.7) and Clinical Pharmacology (12.3)].

9 DRUG ABUSE AND DEPENDENCE

9.1 Controlled Substance

Venlafaxine Extended-Release Tablets contains venlafaxine which is not a controlled substance.

9.2 Abuse

Abuse is the intentional, non-therapeutic use of a drug, even once, for its desirable psychological or physiological effects.

While venlafaxine has not been systematically studied in clinical studies for its potential for abuse, there was no indication of drug-seeking behavior in the clinical studies. However, it is not possible to predict on the basis of premarketing experience the extent to which a CNS-active drug will be misused, diverted, and/or abused once marketed. Consequently, providers should carefully evaluate patients for history of drug abuse and follow such patients closely, observing them for signs of misuse or abuse of venlafaxine (e.g., development of tolerance, incrementation of dose, drug-seeking behavior).

9.3 Dependence

Physical dependence is a state that develops as a result of physiological adaptation in response to repeated drug use, manifested by withdrawal signs and symptoms after abrupt discontinuation or a significant dose reduction of a drug.

In vitro studies revealed that venlafaxine has virtually no affinity for opiate, benzodiazepine, phencyclidine (PCP), or N-methyl-D-aspartic acid (NMDA) receptors.

Venlafaxine was not found to have any significant CNS stimulant activity in rodents. In primate drug discrimination studies, venlafaxine showed no significant stimulant or depressant abuse liability.

Discontinuation effects have been reported in patients receiving venlafaxine [see Dosage and Administration (2.8) and Warnings and Precautions (5.7)].

10 OVERDOSAGE

Human Experience

During the premarketing evaluations of venlafaxine extended-release capsules and immediate-release venlafaxine tablets (for MDD), there were twenty reports of acute overdosage with immediate-release venlafaxine tablets (6 and 14 reports in venlafaxine extended-release capsules and immediate-release venlafaxine tablets patients, respectively), either alone or in combination with other drugs and/or alcohol.

Somnolence was the most commonly reported symptom. Among the other reported symptoms were paresthesia of all four limbs, moderate dizziness, nausea, numb hands and feet, and hot-cold spells 5 days after the overdose. In most cases, no signs or symptoms were associated with overdose. The majority of the reports involved ingestion in which the total dose of venlafaxine taken was estimated to be no more than several-fold higher than the usual therapeutic dose. One patient who ingested 2.75 g of venlafaxine was observed to have two generalized convulsions and a prolongation of QTc to 500 msec, compared with 405 msec at baseline. Mild sinus tachycardia was reported in two of the other patients.

Actions taken to treat the overdose included no treatment, hospitalization and symptomatic treatment, and hospitalization plus treatment with activated charcoal. All patients recovered.

In postmarketing experience, overdose with venlafaxine has occurred predominantly in combination with alcohol and/or other drugs. The most commonly reported events in overdosage include tachycardia, changes in level of consciousness (ranging from somnolence to coma), mydriasis, seizures, and vomiting. Electrocardiogram changes (e.g., prolongation of QT interval, bundle branch block, QRS prolongation), ventricular tachycardia, bradycardia, hypotension, rhabdomyolysis, vertigo, liver necrosis, serotonin syndrome, and death have been reported.

Published retrospective studies report that venlafaxine overdosage may be associated with an increased risk of fatal outcomes compared to that observed with SSRI antidepressant products, but lower than that for tricyclic antidepressants. Epidemiological studies have shown that venlafaxine-treated patients have a higher preexisting burden of suicide risk factors than SSRI-treated patients. The extent to which the finding of an increased risk of fatal outcomes can be attributed to the toxicity of venlafaxine in overdosage, as opposed to some characteristic(s) of venlafaxine-treated patients, is not clear. Prescriptions for Venlafaxine Extended-Release Tablets should be written for the smallest quantity of tablets consistent with good patient management, in order to reduce the risk of overdose.

Management of Overdosage

No specific antidotes for Venlafaxine Extended-Release Tablets are known. In managing overdosage, consider the possibility of multiple drug involvement. Consider contacting a Poison Center (1-800-222-1222) or a medical toxicologist for overdosage management recommendations for Venlafaxine Extended-Release Tablets.

11 DESCRIPTION

Venlafaxine Extended-Release Tablets contains venlafaxine, an SNRI, present as venlafaxine besylate monohydrate salt.

Venlafaxine besylate monohydrate is designated (R/S)-1-[2-(dimethylamino)-1-(4-methoxyphenyl)ethyl] cyclohexanol benzene sulfonate monohydrate or Cyclohexanol, 1-[2-(dimethylamino)-1-(4-methoxyphenyl)ethyl]-, benzenesulfonate, monohydrate and has the molecular formula of C23H33NO5S⸱H2O. Its molecular weight is 453.59. The structural formula is shown as follows:

Venlafaxine besylate is a white to almost white crystalline powder, with a solubility of about 32 mg/ml in water. Its octanol:water partition coefficient is 0.154.

Drug release is controlled by a combination of diffusion through the extended-release coating and erosion of the core tablets. The modified drug release is pH independent.

Venlafaxine Extended-Release Tablets are intended for oral administration and contains 183.95 mg of venlafaxine besylate monohydrate equivalent to 112.5 mg of venlafaxine.

Inactive ingredients: ammonio methacrylate copolymer, hypromellose, lactose monohydrate, magnesium stearate, microcrystalline cellulose, polyethylene glycol, povidone, silicon dioxide, simethicone, talc, titanium dioxide, and triacetin. The tablet printing ink is composed of ammonium hydroxide, black iron oxide, n-butyl alcohol, isopropyl alcohol, propylene glycol, and shellac.

12 CLINICAL PHARMACOLOGY

12.1 Mechanism of Action

The mechanism of action of venlafaxine in treatment of MDD and GAD is unclear, but is thought to be related to the potentiation of serotonin and norepinephrine in the central nervous system, through inhibition of reuptake of serotonin and norepinephrine.

12.2 Pharmacodynamics

In-Vitro studies have demonstrated that venlafaxine and its active metabolite, O-desmethylvenlafaxine (ODV), are potent and selective inhibitors of neuronal serotonin and norepinephrine reuptake and weak inhibitors of dopamine reuptake. Venlafaxine and ODV have no significant affinity for muscarinic-cholinergic, H1-histaminergic, or α1-adrenergic receptors in vitro. Pharmacologic activity at these receptors is hypothesized to be associated with the various anticholinergic, sedative, and cardiovascular effects seen with other psychotropic drugs. Venlafaxine and ODV do not possess monoamine oxidase (MAO) inhibitory activity.

Cardiac Electrophysiology

The effect of venlafaxine on the QT interval was evaluated in a randomized, double-blind, placebo- and positive-controlled three-period crossover thorough QT study in 54 healthy adult subjects. No significant QT prolongation effect of venlafaxine 450 mg (2 times the maximum recommended dosage) was detected.

12.3 Pharmacokinetics

Following single doses of Venlafaxine Extended-Release Tablets under fed conditions, the dose-normalized geometric mean area under curve (AUC) of venlafaxine and ODV were 93.21% and 93.14%, respectively, and the dose-normalized geometric mean peak concentration (Cmax) of venlafaxine and ODV were 93.27% and 106.3%, respectively, compared to those following venlafaxine extended-release capsules under fed conditions.

Steady-state plasma concentrations of venlafaxine and ODV are attained within 3 days of oral multiple-dose therapy.

Absorption

The absolute bioavailability of venlafaxine extended-release capsule is approximately 45%. Following a 112.5 mg Venlafaxine Extended-Release Tablets under fed conditions, the median time to attain Cmax (Tmax) was 10 hours (range 5-18 hours) for venlafaxine and 18 hours (range 5-28 hours) for ODV.

Effect of Food

Ingestion of a high-fat meal with Venlafaxine Extended-Release Tablets increases mean AUC of venlafaxine and ODV by 18% and 17%, respectively; increases mean Cmax of venlafaxine and ODV by 35% and 22%, respectively. Median Tmax was altered by food (median Tmax was 24 hours for both venlafaxine and ODV under fasted conditions).

Distribution

At therapeutic concentrations, venlafaxine and ODV are minimally bound to plasma proteins (27% and 30%, respectively). Administration of Venlafaxine Extended-Release Tablets to a patient taking another drug that is highly protein-bound should not cause increased free concentrations of the other drug. Following a single 112.5 mg dose of Venlafaxine Extended-Release Tablets, the mean apparent volume of distribution (Vz/F) of venlafaxine is 1375 L.

Elimination

Following a single 112.5 mg dose of Venlafaxine Extended-Release Tablets, the mean apparent clearance (CL/F) of venlafaxine is 170 L/hour and the mean elimination half-life (t1/2) of venlafaxine and ODV are 6.8 ± 1.6 hours and 11.3 ± 2.3 hours, respectively.

Metabolism

Following absorption, venlafaxine undergoes extensive pre-systemic metabolism in the liver, primarily to ODV, but also to N-desmethylvenlafaxine, N,O-didesmethylvenlafaxine, and other minor metabolites. In vitro studies indicate that the formation of ODV is catalyzed by CYP2D6; this has been confirmed in a clinical study showing that poor metabolizers of CYP2D6 had increased levels of venlafaxine and reduced levels of ODV compared to extensive metabolizers (Figure 1).

Excretion

Approximately 87% of a venlafaxine dose is recovered in the urine within 48 hours as unchanged venlafaxine (5%), unconjugated ODV (29%), conjugated ODV (26%), or other minor inactive metabolites (27%). Renal elimination of venlafaxine and its metabolites is the primary route of excretion.

Specific Population

A population pharmacokinetic analysis of patients from two studies receiving immediate-release venlafaxine tablets involving both twice daily and three times daily regimens showed that dose-normalized trough plasma levels of either venlafaxine or ODV were unaltered by age or gender differences.

Exposures of venlafaxine and ODV in specific populations are summarized in Figure 1.

Figure 1: Pharmacokinetics of Venlafaxine and Active Metabolite O-Desmethylvenlafaxine (ODV) in Special Populations.

Abbreviations: ODV, O-desmethylvenlafaxine; AUC, area under the curve; Cmax, peak plasma concentrations; *Similar effect is expected with strong CYP2D6 inhibitors

Drug Interaction Studies

Effects of other drugs on the exposure of venlafaxine and ODV are summarized in Figure 2.

Figure 2: Effect of Interacting Drugs on the Pharmacokinetics of Venlafaxine and Active Metabolite O-desmethylvenlafaxine (ODV).

Abbreviations: ODV, O-desmethylvenlafaxine; AUC, area under the curve; Cmax, peak plasma concentrations; EM's, extensive metabolizers; PM's, poor metabolizers
* No dose adjustment on co-administration with CYP2D6 inhibitors.

Effects of venlafaxine on the exposure of other drugs are summarized in Figure 3.

Figure 3: Effect of Venlafaxine on the Pharmacokinetics of Interacting Drugs and Their Active Metabolites.

Abbreviations: AUC, area under the curve; Cmax, peak plasma concentrations; OH, hydroxyl
* Data for 2-OH desipramine were not plotted to enhance clarity; the fold change and 90% CI for Cmax and AUC of 2-OH desipramine were 6.6 (5.5, 7.9) and 4.4 (3.8, 5.0), respectively.

Alcohol: An in vitro study showed significant increase of venlafaxine release from Venlafaxine Extended-Release Tablets at 6 hours with approximately 100% of the drug release in the presence of 40% and 20% alcohol, respectively [see Drug Interactions (7.1)]. Effects of 5% and 10% alcohol on drug release were not significant compared to 0% alcohol. There is no in vivo study conducted for the effect of alcohol on drug exposure.

13 NONCLINICAL TOXICOLOGY

13.1 Carcinogenesis, Mutagenesis, Impairment of Fertility

Carcinogenesis

Tumors were not increased by venlafaxine treatment in mice or rats. Venlafaxine was given by oral gavage to mice for 18 months at doses up to 120 mg/kg per day, which was 1.7 times the maximum recommended human dose on a mg/m^2 basis. Venlafaxine was also given to rats by oral gavage for 24 months at doses up to 120 mg/kg per day. In rats receiving the 120 mg/kg dose, plasma concentrations of venlafaxine at necropsy were 1 times (male rats) and 6 times (female rats) the plasma concentrations of patients receiving the maximum recommended human dose. Plasma levels of the ODV were lower in rats than in patients receiving the maximum recommended dose. ODV, the major human metabolite of venlafaxine, administered by oral gavage to mice and rats for 2 years did not increase the incidence of tumors in either study. Mice received ODV at dosages up to 500/300 mg/kg/day (dosage lowered after 45 weeks of dosing). The exposure at the 300 mg/kg/day dose is 9 times that of a human dose of 225 mg/day. Rats received ODV at dosages up to 300 mg/kg/day (males) or 500 mg/kg/day (females). The exposure at the highest dose is approximately 8 (males) or 11 (females) times that of a human dose of 225 mg/day.

Mutagenesis

Venlafaxine and the major human metabolite, ODV, were not mutagenic in the Ames reverse mutation assay in Salmonella bacteria or the Chinese hamster ovary/HGPRT mammalian cell forward gene mutation assay. Venlafaxine was also not mutagenic or clastogenic in the in vitro BALB/c-3T3 mouse cell transformation assay, the sister chromatid exchange assay in cultured Chinese hamster ovary cells, or in the in vivo chromosomal aberration assay in rat bone marrow. ODV was not clastogenic in the in vitro Chinese hamster ovary cell chromosomal aberration assay or in the in vivo chromosomal aberration assay in rats.

Impairment of Fertility

Reproduction and fertility studies of venlafaxine in rats showed no adverse effects of venlafaxine on male or female fertility at oral doses of up to 2 times the maximum recommended human dose of 225 mg/day on a mg/m^2 basis. However, when desvenlafaxine succinate, the major human metabolite of venlafaxine, was administered orally to male and female rats, fertility was reduced at the high dose of 300 mg/kg/day, which is 10 (males) and 19 (females) times the AUC exposure at an adult human dose of 100 mg per day. There was no effect on fertility at 100 mg/kg/day, which is 3 (males) or 5 (females) times the AUC exposure at an adult human dose of 100 mg per day. These studies did not address reversibility of the effect on fertility. The relevance of these findings to humans is not known.

14 CLINICAL STUDIES

14.1 Major Depressive Disorder

The efficacy of Venlafaxine Extended-Release Tablets for the treatment of major depressive disorder (MDD) in adult patients is based upon adequate and well-controlled studies of venlafaxine extended-release capsules. The results of these adequate and well-controlled studies of venlafaxine extended-release capsules are presented below.

The efficacy of venlafaxine extended-release capsules as a treatment for Major Depressive Disorder (MDD) was established in two placebo-controlled, short-term (8 weeks for study 1; 12 weeks for study 2), flexible-dose studies, with doses starting at 75 mg per day and ranging to 225 mg per day in adult outpatients meeting DSM-III-R or DSM-IV criteria for MDD [Venlafaxine Extended-Release Tablets are only available in 112.5 mg dosage strength]. In moderately depressed outpatients, the initial dose of venlafaxine was 75 mg per day. In both studies, venlafaxine extended-release capsules demonstrated superiority over placebo on the primary efficacy measure defined as change from baseline in the HAM-D-21 total score to the endpoint visit. Venlafaxine extended-release capsules also demonstrated superiority over placebo on the key secondary efficacy endpoint, the Clinical Global Impressions (CGI) Severity of Illness scale. Examination of gender subsets of the population studied did not reveal any differential responsiveness on the basis of gender.

In a longer-term study, adult outpatients with MDD who had responded during an 8-week open-label study on venlafaxine extended-release capsules 75 mg, 150 mg, or 225 mg, once daily every morning were randomized to continuation of their same venlafaxine extended-release capsules dose or to placebo, for up to 26 weeks of observation for relapse. Response during the open-label phase was defined as a CGI Severity of Illness item score of ≤3 and a HAM-D-21 total score of ≤10 at the day 56 evaluation. Relapse during the double-blind phase was defined as follows: (1) a reappearance of major depressive disorder as defined by DSM-IV criteria and a CGI Severity of Illness item score of ≥4 (moderately ill), (2) 2 consecutive CGI Severity of Illness item scores of ≥4, or (3) a final CGI Severity of Illness item score of ≥4 for any patient who withdrew from the study for any reason. Patients receiving continued venlafaxine extended-release capsules treatment experienced statistically significantly lower relapse rates over the subsequent 26 weeks compared with those receiving placebo.

Table 15: Primary Efficacy Results for Studies in Major Depressive Disorder in Adults (Studies 1 and 2)
Study number | Treatment Group | Primary Efficacy Measure: HAM-D Score
 |  | Mean Baseline Score (SD) | LS Mean Change from Baseline | Placebo Subtracted Differenceb (95%CI)
Study 1 | Venlafaxine extended-release capsules (75 mga, 150 mga, 225 mg per day)* | 24.5 | -11.7 | -4.45 (-6.66,-2.25)
Study 1 | Placebo | 23.6 | -7.24 | -
Study 2 | Venlafaxine extended-release capsules (75 mga, 150 mga, 225 mg per day)* | 24.5 | -15.11 | -6.40 (-8.45,-4.34)
Study 2 | Placebo | 24.9 | -8.71
SD: standard deviation; LS Mean: least-squares mean; CI: confidence interval.
a Venlafaxine Extended-Release Tablets are only available as 112.5 mg dosage strength.
b Difference (drug minus placebo) in least-squares mean change from baseline.
* Doses statistically significantly superior to placebo.

14.2 Generalized Anxiety Disorder

The efficacy of Venlafaxine Extended-Release Tablets for the treatment of Generalized Anxiety Disorder (GAD) in adult patients is based upon adequate and well-controlled studies of venlafaxine extended-release capsules. The results of these adequate and well-controlled studies of venlafaxine extended-release capsules are presented below.

The efficacy of venlafaxine extended-release capsules as a treatment for Generalized Anxiety Disorder (GAD) was established in two 8-week, placebo-controlled, fixed-dose studies of 75 mg to 225 mg per day, one 6-month, placebo-controlled, flexible-dose study of 75 mg to 225 mg per day), and one 6-month, placebo-controlled, fixed-dose study of 37.5 mg, 75 mg, and 150 mg per day in adult outpatients meeting DSM-IV criteria for GAD [Venlafaxine Extended-Release Tablets are only available in 112.5 mg dosage strength].

In one 8-week study, venlafaxine extended-release capsules demonstrated superiority over placebo for the 75 mg, 150 mg, and 225 mg per day doses as measured by the Hamilton Rating Scale for Anxiety (HAM-A) total score, both the HAM-A anxiety and tension items, and the Clinical Global Impressions (CGI) scale. However, the 75 mg and 150 mg per day doses were not as consistently effective as the highest dose (Study 1). A second 8-week study evaluating doses of 75 mg and 150 mg per day and placebo showed that both doses were more effective than placebo on some of these same outcomes; however, the 75 mg per day dose was more consistently effective than the 150 mg per day dose (Study 2). A dose-response relationship for effectiveness in GAD was not clearly established in the 75 mg to 225 mg per day dose range studied.

Two 6-month studies, one evaluating venlafaxine extended-release capsules doses of 37.5 mg, 75 mg, and 150 mg per day (study 3) and the other evaluating venlafaxine extended-release capsules doses of 75 mg to 225 mg per day (study 4), showed that daily doses of 75 mg or higher were more effective than placebo on the HAM-A total, both the HAM-A anxiety and tension items, and the CGI scale during 6 months of treatment. While there was also evidence for superiority over placebo for the 37.5 mg per day dose, this dose was not as consistently effective as the higher doses.

Examination of gender subsets of the population studied did not reveal any differential responsiveness on the basis of gender.

Table 16: Primary Efficacy Results for Studies in Generalized Anxiety Disorder in Adults (Studies 1, 2, 3, and 4)
Study Number | Treatment Group | Primary Efficacy Measure: HAM-A Score
 |  | Mean Baseline Score (SD) | LS Mean Change from Baseline (SE)* | Placebo Subtracted Differenceb (95% CI)
Study 1 | Venlafaxine extended-release capsules 75 mga | 24.7 | -11.1 (0.95) | -1.5 (-3.8, 0.8)
Study 1 | 150 mga | 24.5 | -11.7 (0.87) | -2.2 (-4.5, 0.1)
Study 1 | 225 mg | 23.6 | -12.1 (0.81) | -2.6 (-4.9, -0.3)
Study 1 | Placebo | 24.1 | -9.5 (0.85)
Study 2 | Venlafaxine extended-release capsules 75 mga | 23.7 | -10.6 (0.82) | -2.6 (-4.6, -0.5)
Study 2 | 150 mga | 23.0 | -9.8 (0.86) | -1.7 (-3.8, 0.3)
Study 2 | Placebo | 23.7 | -8.0 (0.73)
Study 3 | Venlafaxine extended-release capsules 37.5 mga | 26.6 (0.4) | -13.8 | -2.8 (-5.1, -0.6)
Study 3 | 75 mga | 26.3 (0.4) | -15.5 | -4.6 (-6.9, -2.3)
Study 3 | 150 mga | 26.3 (0.4) | -16.4 | -5.5 (-7.8, -3.1)
Study 3 | Placebo | 26.7 (0.5) | -11.0
Study 4 | Venlafaxine extended-release capsules 75 mga to 225 mg | 25.0 | -13.4 (0.79) | - 4.7 (-6.6, -2.9)
Study 4 | Placebo | 24.9 | -8.7 (0.70)
SD: standard deviation; SE: standard error; LS Mean: least-squares mean; CI: confidence interval.
a Venlafaxine Extended-Release Tablets are only available as 112.5 mg dosage strength.
b Difference (drug minus placebo) in least-squares mean change from baseline.
* Doses statistically significantly superior to placebo.

16 HOW SUPPLIED/STORAGE AND HANDLING

Venlafaxine Extended-Release Tablets are suppled as:

- 112.5 mg, white, round, biconvex tablet, with “ALM” over “632” printed in black ink on one side, and plain on the other side.
  NDC 52427-632-30 Bottle of 30 tablets

Storage and Handling

Store at controlled room temperature 20° to 25°C (68° to 77°F); excursions permitted to 15° to 30°C (59° to 86°F) [see USP Controlled Room Temperature].

17 PATIENT COUNSELING INFORMATION

Advise the patient to read the FDA-approved patient labeling (Medication Guide).

Suicidal Thoughts and Behaviors

Advise patients, and caregivers to look for the emergence of suicidality especially early during treatment and when the dose is adjusted up or down, and instruct them to report such symptoms to the healthcare provider [see Boxed Warning and Warnings and Precautions (5.1)].

Concomitant Medication

Instruct patients not to take Venlafaxine Extended-Release Tablets with an MAOI or within 14 days of stopping an MAOI [see Contraindications (4)].

Serotonin Syndrome

Caution patients about the risk of serotonin syndrome, particularly with the concomitant use of Venlafaxine Extended-Release Tablets with other serotonergic drugs including triptans, tricyclic antidepressants, opioids, lithium, amphetamines, tryptophan, buspirone, St. John’s Wort, and with drugs that impair metabolism of serotonin (in particular, MAOIs, both those intended to treat psychiatric disorders and also others, such as linezolid). Instruct patients to contact their health care provider or report to the emergency room if they experience signs or symptoms of serotonin syndrome [see Warnings and Precautions (5.2) and Drug Interactions (7.1)].

Elevated Blood Pressure

Advise patients that they should have regular monitoring of blood pressure when taking Venlafaxine Extended-Release Tablets [see Warnings and Precautions (5.3)].

Increased Risk of Bleeding

Inform patients about the concomitant use of Venlafaxine Extended-Release Tablets with NSAIDs, aspirin, other antiplatelet drugs, warfarin, or other drugs that affect coagulation because the combined use has been associated with an increased risk of bleeding. Advise patients to inform their health care providers if they are taking or planning to take any prescription or over-the-counter medications that increase the risk of bleeding [see Warnings and Precautions (5.4)].

Activation of Mania/Hypomania

Advise patients, their families and caregivers to observe for signs of activation of mania/hypomania and instruct them to report such symptoms to the healthcare provider [see Warnings and Precautions (5.6)].

Discontinuation Syndrome

Advise patients not to abruptly stop taking Venlafaxine Extended-Release Tablets without talking first with their healthcare provider. Patients should be aware that discontinuation effects may occur when stopping Venlafaxine Extended-Release Tablets and they should monitor for discontinuation symptoms [see Warnings and Precautions (5.7) and Adverse Reactions (6.1)].

Sexual Dysfunction

Advise patients that use of Venlafaxine Extended-Release Tablets may cause symptoms of sexual dysfunction in both male and female patients. Inform patients that they should discuss any changes in sexual function and potential management strategies with their healthcare provider [see Warnings and Precautions (5.13)].

Cardiovascular/Cerebrovascular Disease

Caution is advised in administering Venlafaxine Extended-Release Tablets to patients with cardiovascular, cerebrovascular, or lipid metabolism disorders [see Adverse Reactions (6.1)].

Serum Cholesterol and Triglyceride Elevation

Advise patients that elevations in total cholesterol, LDL and triglycerides may occur and that measurement of serum lipids may be considered [see Warnings and Precautions (6.1)].

Interference with Cognitive and Motor Performance

Caution patients about operating hazardous machinery, including automobiles, until they are reasonably certain that Venlafaxine Extended-Release Tablets therapy does not adversely affect their ability to engage in such activities.

Alcohol

Advise patients to avoid alcohol while taking Venlafaxine Extended-Release Tablets [see Drug Interactions (7.1)].

Allergic Reactions

Advise patients to notify their healthcare provider if they develop allergic phenomena such as rash, hives, swelling, or difficulty breathing [see Contraindications (4) and Adverse Reactions (6.2)].

Pregnancy

Advise patients to notify their healthcare provider if they become pregnant or intend to become pregnant during treatment with Venlafaxine Extended-Release Tablets. Advise patients that Venlafaxine Extended-Release Tablets use during mid to late pregnancy may lead to an increased risk for preeclampsia; may increase the risk for neonatal complications requiring prolonged hospitalization, respiratory support, and tube feeding. Advise patients that there is a pregnancy exposure registry that monitors pregnancy outcomes in women exposed to Venlafaxine Extended-Release Tablets during pregnancy [see Use in Specific Populations (8.1)].

Manufactured by:
Norwich Pharmaceuticals, Inc.
Norwich, NY 13815 USA

Distributed by:
Almatica Pharma LLC
Morristown, NJ 07960 USA

PI632-01

MEDICATION GUIDE

Venlafaxine Extended-Release Tablets (ven'' la fax' een)

for oral use

What is the most important information I should know about Venlafaxine Extended-Release Tablets?

Venlafaxine Extended-Release Tablets may cause serious side effects, including:

- Increased risk of suicidal thoughts and actions. Venlafaxine Extended-Release Tablets and other antidepressant medicines may increase suicidal thoughts and actions in some children, adolescents, and young adults, especially within the first few months of treatment or when the dose is changed. Venlafaxine Extended-Release Tablets is not for use in children.
  - Depression or other serious mental illnesses are the most important causes of suicidal thoughts or actions.
    How can I watch for and try to prevent suicidal thoughts and actions in myself or a family member?
  - Pay close attention to any changes, especially sudden changes, in mood, behavior, actions, thoughts, or feelings. This is very important when an antidepressant medicine is started or when the dose is changed.
  - Call your healthcare provider right away to report new or sudden changes in mood, behavior, thoughts, or feelings.
  - Keep all follow-up visits with your healthcare provider as scheduled. Call your healthcare provider between visits as needed, especially if you have concerns about symptoms.

Call your healthcare provider or get emergency help right away if you or a family member have any of the following symptoms, especially if they are new, worse, or worry you:

- attempts to commit suicide
- acting aggressive, being angry, or violent
- new or worse depression
- panic attacks
- new or worse irritability
- an extreme increase in activity or talking (mania)
- thoughts about suicide or dying
- acting on dangerous impulses
- new or worse anxiety
- feeling very agitated or restless
- trouble sleeping
- other unusual changes in behavior or mood

What is Venlafaxine Extended-Release Tablets?

Venlafaxine Extended-Release Tablets is a prescription medicine used to treat adults with:

- a certain type of depression called Major Depressive Disorder (MDD)
- Generalized Anxiety Disorder (GAD)

It is not known if Venlafaxine Extended-Release Tablets is safe and effective for use in children.

Do not take Venlafaxine Extended-Release Tablets if you:

- are allergic to venlafaxine besylate, venlafaxine hydrochloride, desvenlafaxine succinate, or any of the ingredients in Venlafaxine Extended-Release Tablets. See the end of this Medication Guide for a complete list of ingredients in Venlafaxine Extended-Release Tablets.
- take a Monoamine Oxidase Inhibitor (MAOI)
- have stopped taking an MAOI in the last 14 days
- are being treated with the antibiotic linezolid or intravenous methylene blue

Ask your healthcare provider or pharmacist if you are not sure if you take an MAOI, including MAOIs such as linezolid or intravenous methylene blue.

Do not start taking an MAOI for at least 7 days after you stop treatment with Venlafaxine Extended-Release Tablets.

Before taking Venlafaxine Extended-Release Tablets tell your healthcare provider about all your medical conditions, including if you:

- have, or have a family history of suicide, bipolar disorder, depression, mania or hypomania
- have high blood pressure
- have heart problems
- have cerebrovascular problems or had a stroke
- have or have had bleeding problems
- have high pressure in the eye (glaucoma)
- have high cholesterol or high triglycerides
- have kidney or liver problems
- have or have had seizures or convulsions
- have low sodium levels in your blood
- have lung problems
- drink alcohol
- are pregnant or plan to become pregnant. Venlafaxine Extended-Release Tablets may harm your unborn baby. Talk to your healthcare provider about the risk to you and your unborn baby if you take Venlafaxine Extended-Release Tablets during pregnancy.
  - Tell your healthcare provider right away if you become pregnant or think you are pregnant during treatment with Venlafaxine Extended-Release Tablets.
  - Pregnancy Exposure Registry. There is a pregnancy registry for women who are exposed to Venlafaxine Extended-Release Tablets during pregnancy. The purpose of the registry is to collect information about the health of you and your baby. If you become pregnant during treatment with Venlafaxine Extended-Release Tablets, talk to your healthcare provider about registering with the National Pregnancy Registry for Antidepressants. You can register by calling 1-844-405-6185 or by visiting online at https://womensmentalhealth.org/research/pregnancyregistry/antidepressants.
- are breastfeeding or plan to breastfeed. Venlafaxine passes into your breast milk and may harm your baby. Talk to your healthcare provider about the best way to feed your baby during treatment with Venlafaxine Extended-Release Tablets.

Tell your healthcare provider about all the medicines you take, including prescription and over-the-counter medicines, vitamins, and herbal supplements.

Venlafaxine Extended-Release Tablets and other medicines may affect each other causing possible serious side effects. Venlafaxine Extended-Release Tablets may affect the way other medicines work and other medicines may affect the way Venlafaxine Extended-Release Tablets works.

Especially tell your healthcare provider if you take:

- medicines to treat migraine headaches known as triptans
- tricyclic antidepressants
- lithium
- tramadol, fentanyl, meperidine, methadone, or other opioids
- tryptophan
- buspirone
- amphetamines
- St. John’s Wort
- other medicines containing desvenlafaxine or venlafaxine
- phentermine
- medicines that can affect blood clotting such as aspirin, nonsteroidal anti-inflammatory drugs (NSAIDs), warfarin

Ask your healthcare provider if you are not sure if you are taking any of these medicines. Your healthcare provider can tell you if it is safe to take Venlafaxine Extended-Release Tablets with your other medicines.

Do not start or stop any other medicines during treatment with Venlafaxine Extended-Release Tablets without first talking to your healthcare provider. Stopping Venlafaxine Extended-Release Tablets suddenly may cause you to have serious side effects. See, “What are the possible side effects of Venlafaxine Extended-Release Tablets?”

Know the medicines you take. Keep a list of them to show to your healthcare provider and pharmacist when you get a new medicine.

How should I take Venlafaxine Extended-Release Tablets?

- Take Venlafaxine Extended-Release Tablets exactly as your healthcare provider tells you to. Do not change your dose or stop taking Venlafaxine Extended-Release Tablets without first talking to your healthcare provider.
- Your healthcare provider may need to change the dose of Venlafaxine Extended-Release Tablets until it is the right dose for you.
- Take Venlafaxine Extended-Release Tablets 1 time each day with food.
- Venlafaxine Extended-Release Tablets may be taken either in the morning or in the evening, but you should take it the same way each time.
- Swallow Venlafaxine Extended-Release Tablets whole. Do not divide, crush, chew, or dissolve Venlafaxine Extended-Release Tablets.
- If you take too much Venlafaxine Extended-Release Tablets, call your healthcare provider or poison control center at 1-800-222-1222 or go the nearest hospital emergency room right away.

What should I avoid while taking Venlafaxine Extended-Release Tablets?

- Do not drive, operate heavy machinery, or do other dangerous activities until you know how Venlafaxine Extended-Release Tablets affects you. Venlafaxine Extended-Release Tablets can make you drowsy.
- You should not drink alcohol during treatment with Venlafaxine Extended-Release Tablets. Drinking alcohol during treatment with Venlafaxine Extended-Release Tablets can increase your risk of having serious side effects.

What are the possible side effects of Venlafaxine Extended-Release Tablets?

Venlafaxine Extended-Release Tablets may cause serious side effects, including:

- See “What is the most important information I should know about Venlafaxine Extended-Release Tablets?”
- Serotonin Syndrome. Taking Venlafaxine Extended-Release Tablets can cause a potentially life-threatening problem called serotonin syndrome. The risk of developing serotonin syndrome is increased when Venlafaxine Extended-Release Tablets is taken with certain other medicines. See, “Do not take Venlafaxine Extended-Release Tablets if you:” Stop taking Venlafaxine Extended-Release Tablets and call your healthcare provider or go to the nearest hospital emergency room right away if you have any of the following signs and symptoms of serotonin syndrome:
  - agitation
  - confusion
  - fast heartbeat
  - dizziness
  - flushing
  - tremors, stiff muscles, or muscle twitching
  - seizures
  - seeing or hearing things that are not real (hallucinations)
  - coma
  - changes in blood pressure
  - sweating
  - high body temperature (hyperthermia)
  - loss of coordination
  - nausea, vomiting, diarrhea
- Increases in blood pressure. Your healthcare provider should check your blood pressure before starting treatment and regularly during treatment with Venlafaxine Extended-Release Tablets. If you have high blood pressure, it should be controlled before you start treatment with Venlafaxine Extended-Release Tablets.
- Increased risk of bleeding. Taking Venlafaxine Extended-Release Tablets with aspirin, non-steroidal anti-inflammatory drugs (NSAIDs), or blood thinners may add to this risk. Tell your healthcare provider right away about any unusual bleeding or bruising.
- Eye problems (angle-closure glaucoma). Venlafaxine Extended-Release Tablets may cause a certain type of eye problem called angle-closure glaucoma in people with certain other eye conditions. You may want to undergo an eye examination to see if you are at risk and receive preventative treatment if you are. Call your healthcare provider if you have eye pain, changes in your vision, or swelling or redness in or around the eye.
- Manic episodes. Manic episodes may happen in people with bipolar disorder who take Venlafaxine Extended-Release Tablets. Symptoms may include:
  - greatly increased energy
  - racing thoughts
  - unusually grand ideas
  - talking more or faster than usual
  - severe trouble sleeping
  - reckless behavior
  - excessive happiness or irritability
- Discontinuation syndrome. Suddenly stopping Venlafaxine Extended-Release Tablets may cause you to have serious side effects. Your healthcare provider may want to decrease your dose slowly. Symptoms may include:
  - dizziness
  - irritability and agitation
  - anxiety
  - sweating
  - seizures
  - ringing in your ears (tinnitus)
  - nausea
  - problems sleeping
  - tiredness
  - confusion
  - electric shock sensation (paresthesia)
  - headache
  - diarrhea
  - abnormal dreams
  - changes in your mood
  - hypomania
- Seizures (convulsions).
- Low sodium levels in your blood (hyponatremia). Low sodium levels in your blood may be serious and may cause death. Elderly people may be at greater risk for this. Signs and Symptoms of low sodium levels in your blood may include:
  - headache
  - difficulty concentrating
  - memory changes
  - confusion
  - weakness and unsteadiness on your feet which can lead to falls
  In severe or more sudden cases, signs and symptoms include:
  - hallucinations (seeing or hearing things that are not real)
  - fainting
  - seizures
  - coma
  - respiratory arrest
- Lung problems. Some people who have taken the medicine venlafaxine which is the same kind of medicine as the medicine in Venlafaxine Extended-Release Tablets have had lung problems. Symptoms of lung problems include difficulty breathing, cough, or chest discomfort. Tell your healthcare provider right away if you have any of these symptoms.
- Sexual problems (dysfunction). Taking selective serotonin reuptake inhibitors (SNRIs), including Venlafaxine Extended-Release Tablets, may cause sexual problems.
  Symptoms in males may include:
  - delayed ejaculation or inability to have an ejaculation
  - decreased sex drive
  - problems getting or keeping an erection
  Symptoms in females may include:
  - decreased sex drive
  - delayed orgasm or inability to have an orgasm
  Talk to your healthcare provider if you develop any changes in your sexual function or if you have any questions or concerns about sexual problems during treatment with Venlafaxine Extended-Release Tablets. There may be treatments your healthcare provider can suggest.

Your healthcare provider may tell you to stop taking Venlafaxine Extended-Release Tablets if you develop serious side effects during treatment with Venlafaxine Extended-Release Tablets.

The most common side effects of Venlafaxine Extended-Release Tablets include:

- nausea
- dry mouth
- male and female sexual problems
- loss of appetite (anorexia)
- sleepiness
- sweating
- constipation

These are not all the possible side effects of Venlafaxine Extended-Release Tablets.

Call your doctor for medical advice about side effects. You may report side effects to FDA at 1-800-FDA-1088.

How should I store Venlafaxine Extended-Release Tablets?

- Store Venlafaxine Extended-Release Tablets at room temperature between 68°F to 77°F (20°C to 25°C).
- Keep Venlafaxine Extended-Release Tablets in a dry place.

Keep Venlafaxine Extended-Release Tablets and all medicines out of the reach of children.

General information about the safe and effective use of Venlafaxine Extended-Release Tablets.

Medicines are sometimes prescribed for purposes other than those listed in a Medication Guide. Do not use Venlafaxine Extended-Release Tablets for a condition for which it was not prescribed. Do not give Venlafaxine Extended-Release Tablets to other people, even if they have the same symptoms that you have. It may harm them. You may ask your healthcare provider or pharmacist for information about Venlafaxine Extended-Release Tablets that is written for healthcare professionals.

What are the ingredients in Venlafaxine Extended-Release Tablets?

Active ingredient: venlafaxine besylate monohydrate

Inactive ingredients: ammonio methacrylate copolymer, hypromellose, lactose monohydrate, magnesium stearate, microcrystalline cellulose, polyethylene glycol, povidone, silicon dioxide, simethicone, talc, titanium dioxide, and triacetin. The tablets printing ink is composed of ammonium hydroxide, black iron oxide, n-butyl alcohol, isopropyl alcohol, propylene glycol, and shellac.

Manufactured by: Norwich Pharmaceuticals, Inc., Norwich, NY 13815 USA

Distributed by: Almatica Pharma LLC, Morristown, NJ 07960 USA

For more information about Venlafaxine Extended-Release Tablets call 1-877-447-7979.

This Medication Guide has been approved by the U.S. Food and Drug Administration.

Revised: 8/2023

PL632-01

PACKAGE LABEL PRINCIPAL DISPLAY PANEL SECTION

NDC 52427-632-30

Venlafaxine Extended-Release Tablets

112.5 mg

PHARMACIST: Dispense the accompanying Medication Guide to each patient.

Rx only

30 Tablets